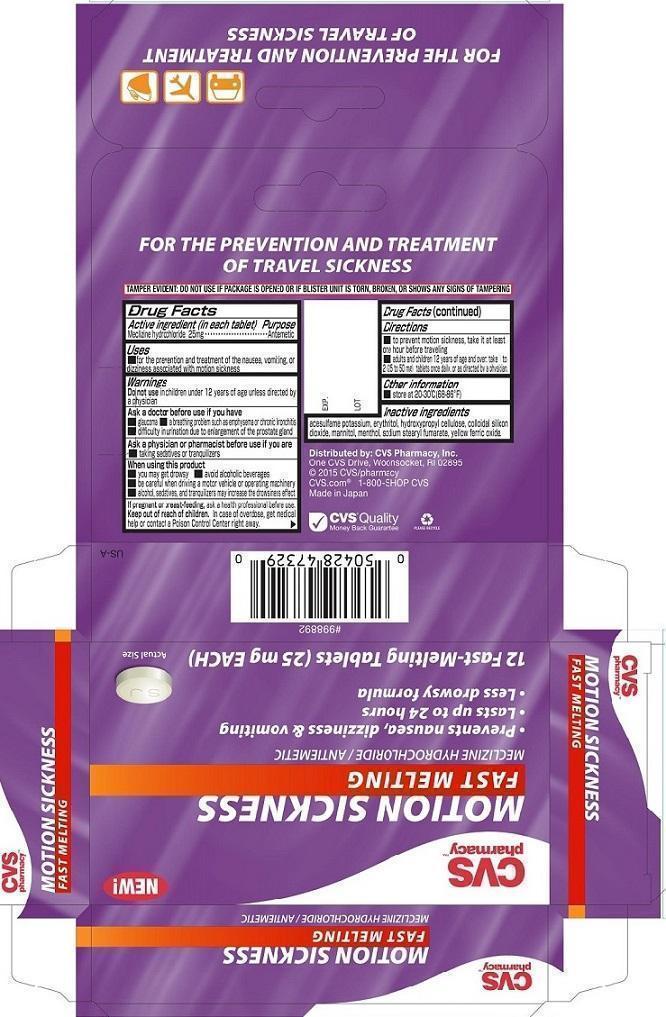 DRUG LABEL: CVS Motion Sickness Fast Melting
NDC: 59779-534 | Form: TABLET, ORALLY DISINTEGRATING
Manufacturer: CVS Pharmacy, Inc.
Category: otc | Type: HUMAN OTC DRUG LABEL
Date: 20251230

ACTIVE INGREDIENTS: MECLIZINE HYDROCHLORIDE 25 mg/1 1
INACTIVE INGREDIENTS: HYDROXYPROPYL CELLULOSE, UNSPECIFIED; SILICON DIOXIDE; ERYTHRITOL; MANNITOL; ACESULFAME POTASSIUM; FERRIC OXIDE YELLOW; SODIUM STEARYL FUMARATE; LEVOMENTHOL

CVS Motion Sickness Fast Melting (PLD)

Active ingredient (in each tablet)
Meclizine hydrochloride 25mg

Purpose
Meclizine hydrochloride Antiemetic

Uses
■ For the prevention and treatment of the nausea, vomiting, or dizziness associated with motion sickness.

Warnings

Do not use in children under 12 years of age unless directed by a physician

Ask a doctor before use if you have
■ glaucoma ■ a breathing problem such as emphysema or chronic bronchitis
■ difficulty in urination due to enlargement of the prostate gland

ASK DOCTOR/PHARMACIST

Ask a physician or pharmacist before use if you are
■ taking sedatives or tranquilizers

When using this product
■ you may get drowsy ■ avoid alcoholic beverages
■ be careful when driving a motor vehicle or operating machinery
■ alcohol, sedatives, and tranquilizers may increase the drowsiness effect

PREGNANCY OR BREAST FEEDING

If pregnant or breast-feeding, ask a health professional before use.

Keep out of reach of children. In case of overdose, get medical help or contact a Poison Control Center right away.

Directions
To prevent motion sickness take it at least one hour before traveling
Adults and children 12 years of age and over: take 1 to 2 (25 to 50 mg) tablets once daily, or as directed by a physician.

Other information
■ Store at 20-30°C (68-86°F)

Inactive ingredients
acesulfame potassium, erythritol, hydroxypropyl cellulose, colloidal silicon dioxide, mannitol, menthol, sodium stearyl fumarate, yellow ferric oxide.